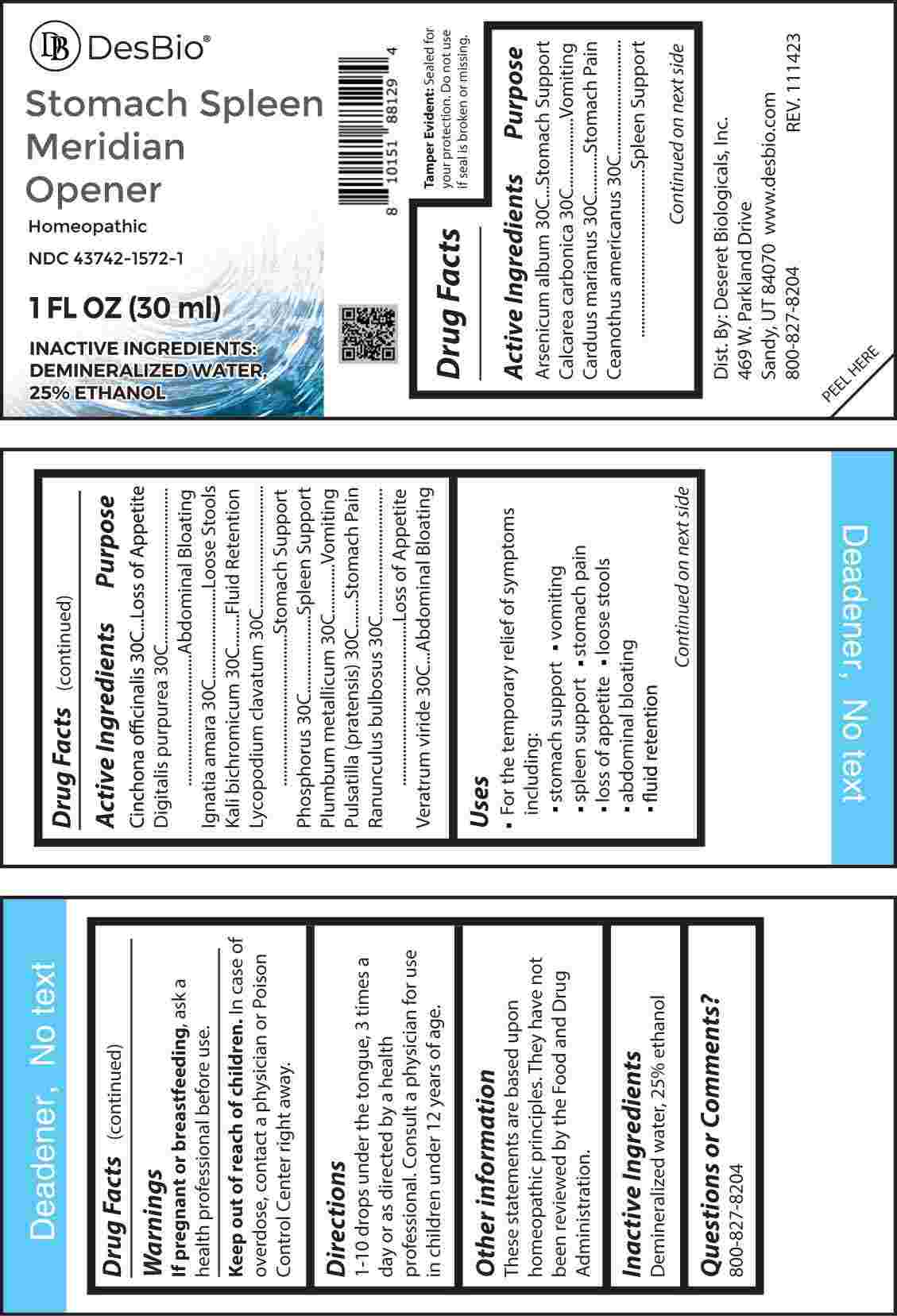 DRUG LABEL: Stomach Spleen Meridian Opener
NDC: 43742-1572 | Form: LIQUID
Manufacturer: Desert Biologicals, Inc.
Category: homeopathic | Type: HUMAN OTC DRUG LABEL
Date: 20240221

ACTIVE INGREDIENTS: ARSENIC TRIOXIDE 30 [hp_C]/1 mL; OYSTER SHELL CALCIUM CARBONATE, CRUDE 30 [hp_C]/1 mL; SILYBUM MARIANUM SEED 30 [hp_C]/1 mL; CEANOTHUS AMERICANUS LEAF 30 [hp_C]/1 mL; CINCHONA OFFICINALIS BARK 30 [hp_C]/1 mL; DIGITALIS 30 [hp_C]/1 mL; STRYCHNOS IGNATII SEED 30 [hp_C]/1 mL; POTASSIUM DICHROMATE 30 [hp_C]/1 mL; LYCOPODIUM CLAVATUM SPORE 30 [hp_C]/1 mL; PHOSPHORUS 30 [hp_C]/1 mL; LEAD 30 [hp_C]/1 mL; PULSATILLA PRATENSIS WHOLE 30 [hp_C]/1 mL; RANUNCULUS BULBOSUS WHOLE 30 [hp_C]/1 mL; VERATRUM VIRIDE ROOT 30 [hp_C]/1 mL
INACTIVE INGREDIENTS: WATER; ALCOHOL

DRUG FACTS:

ACTIVE INGREDIENTS:

Arsenicum Album 30C, Calcarea Carbonica 30C, Carduus Marianus 30C, Ceanothus Americanus 30C, Cinchona Officinalis 30C, Digitalis Purpurea 30C, Ignatia Amara 30C, Kali Bichromicum 30C, Lycopodium Clavatum 30C, Phosphorus 30C, Plumbum Metallicum 30C, Pulsatilla (Pratensis) 30C, Ranunculus Bulbosus 30C, Veratrum Viride 30C.

PURPOSE:

Arsenicum Album – Stomach Support, Calcarea Carbonica - Vomiting, Carduus Marianus – Stomach Pain, Ceanothus Americanus – Spleen Support, Cinchona Officinalis – Loss of Appetite, Digitalis Purpurea – Abdominal Bloating, Ignatia Amara – Loose Stools, Kali Bichromicum – Fluid Retention, Lycopodium Clavatum – Stomach Support, Phosphorus – Spleen Support, Plumbum Metallicum - Vomiting, Pulsatilla (Pratensis) – Stomach Pain, Ranunculus Bulbosus – Loss of Appetite, Veratrum Viride – Abdominal Bloating

USES:

• For the temporary relief of symptoms including:

• stomach support • vomiting • spleen support

• stomach pain • loss of appetite • loose stools

• abdominal bloating • fluid retention

These statements are based upon homeopathic principles. They have not been reviewed by the Food and Drug Administration.

WARNINGS:

If pregnant or breast-feeding, ask a health professional before use.

Keep out of reach of children. In case of overdose, contact a physician or Poison Control Center right away.
Tamper Evident: Sealed for your protection. Do not use if seal is broken or missing.

KEEP OUT OF REACH OF CHILDREN:

In case of overdose, contact a physician or Poison Control Center right away.

DIRECTIONS:

1-10 drops under the tongue, 3 times a day or as directed by a health professional. Consult a physician for use in children under 12 years of age.

INACTIVE INGREDIENTS:

Demineralized water, 25% ethanol.

QUESTIONS:

Dist. By: Deseret Biologicals, Inc.
469 W. Parkland Drive
Sandy, UT 84070

www.desbio.com

800-827-8204

PACKAGE LABEL DISPLAY:

Des Bio

Stomach Spleen

Meridian Opener

Homeopathic

NDC 43742-1572-1

1 FL OZ (30 ml)